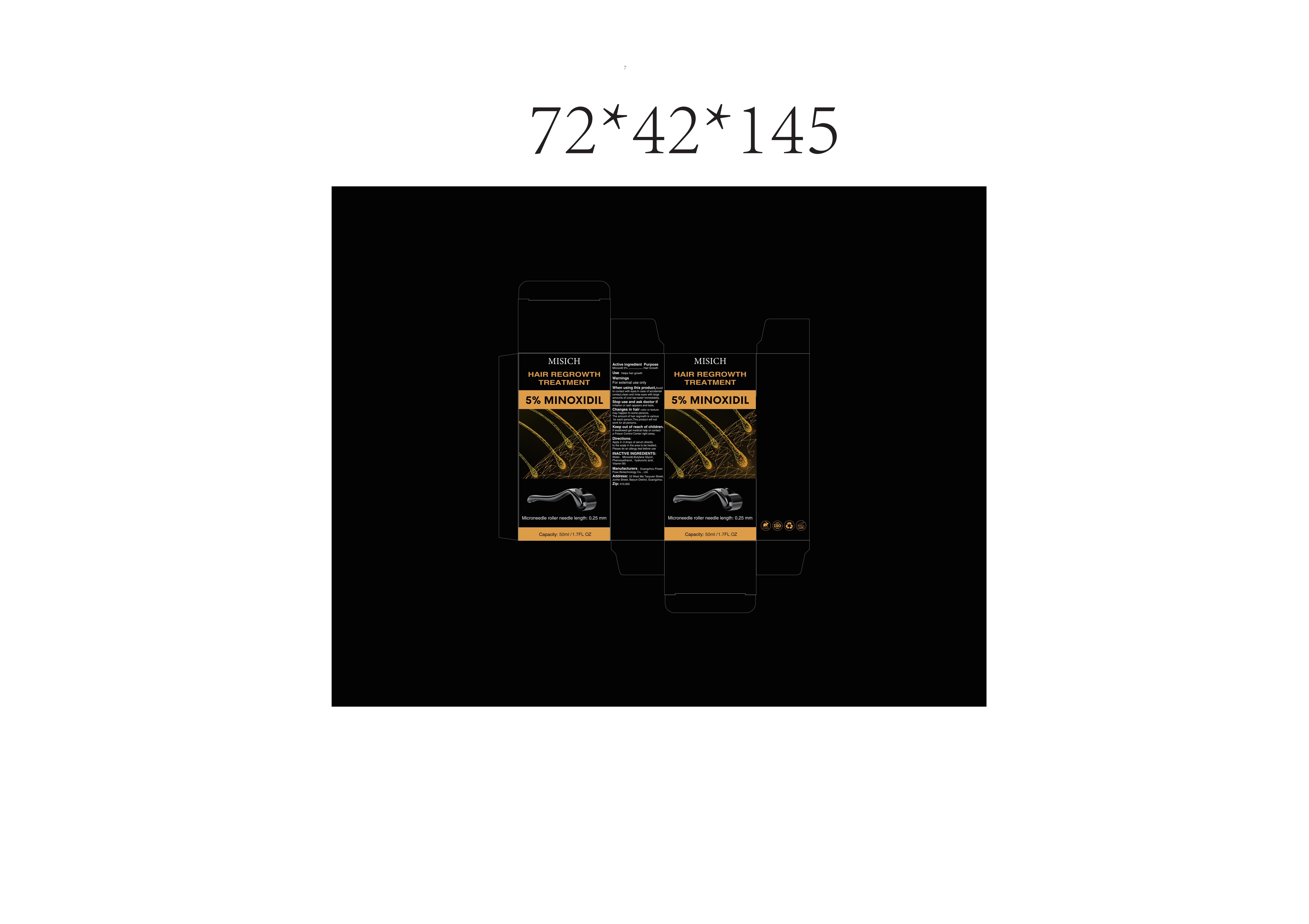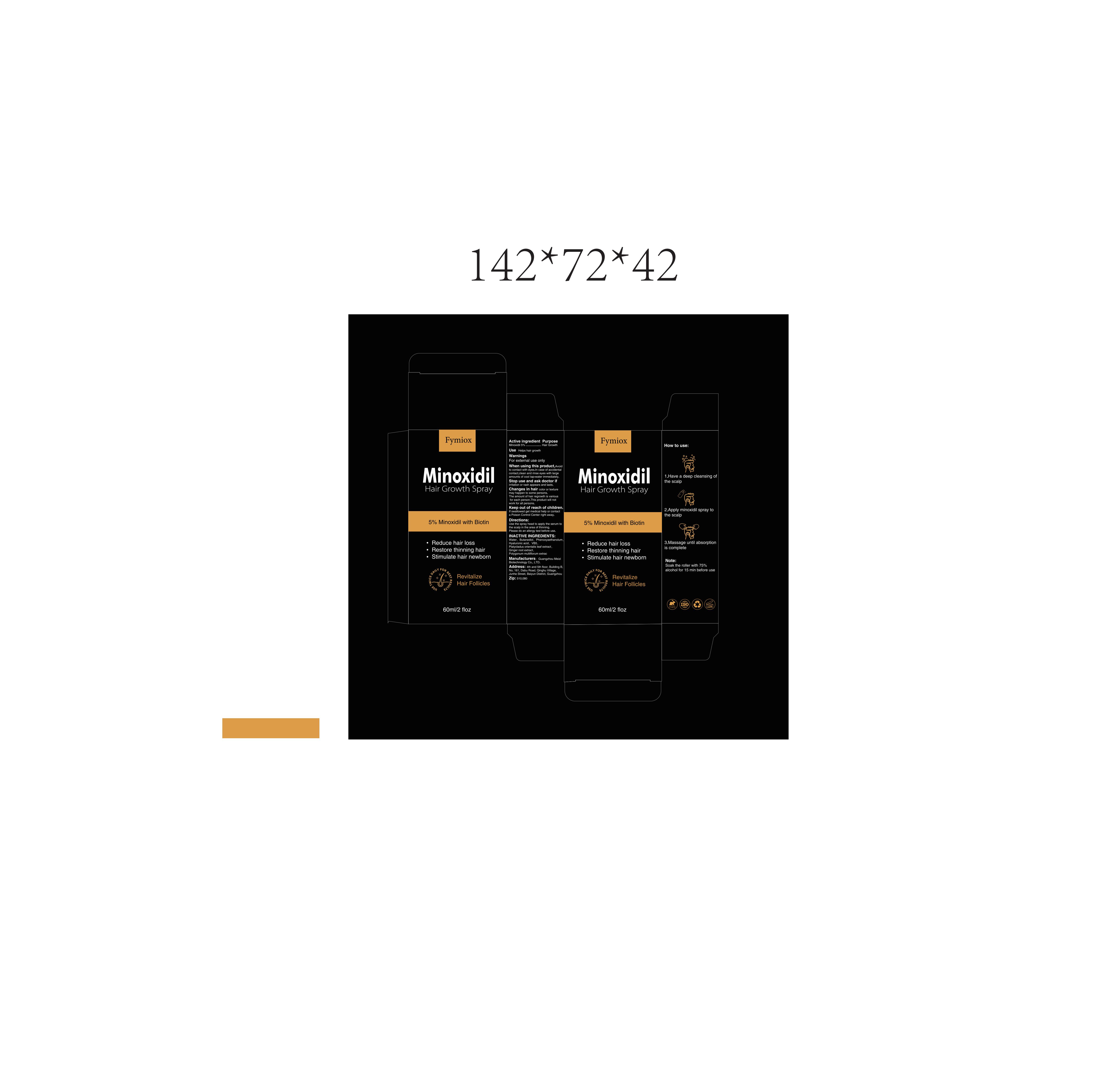 DRUG LABEL: Fymiox Minoxidil Hair Growth Spray.
NDC: 84213-001 | Form: SPRAY
Manufacturer: Shenzhen Weilaiwang Technology Co., Ltd
Category: otc | Type: HUMAN OTC DRUG LABEL
Date: 20240327

ACTIVE INGREDIENTS: MINOXIDIL 5 g/100 mL
INACTIVE INGREDIENTS: WATER; BUTANEDIOL (MIXED ISOMERS); HYALURONIC ACID; GINGER; REYNOUTRIA MULTIFLORA ROOT OIL; PLATYCLADUS ORIENTALIS LEAF; PANTOTHENIC ACID; ANISOLE

84213-001

Active Ingredient

Minoxidil 5%

Purpose

Hair Growth

Use

Helps hair growth

Warnings

For external use only

Do not use on injured skin

When Using

When using this product,Avoid to contact with eyes.In case of accidental contact,clean and rinse eyes with large amounts of cool tap-water immediately.

Stop Use

Stop use and ask doctor if irritation or rash appears and lasts.

Ask Doctor

Changes in hair color or texture may happen to some persons.

Keep Oot Of Reach Of Children

The amount of hair regrowth is various for each person.This product will not work for all persons.
Keep out of reach of children. If swallowed get medical help or contact a Poison Control Center right away.

Directions

Use the spray head to apply the serum to the scalp in the area of thinning
Please do an allergy test before use

Other information

Please do an allergy test before use

Inactive ingredients

Water, Butanediol, Phenoxyaethanolum, Hyaluronic acid, VB5, Platycladus orientalis leaf extract, Ginger root extract, Polygonum multiflorum extract